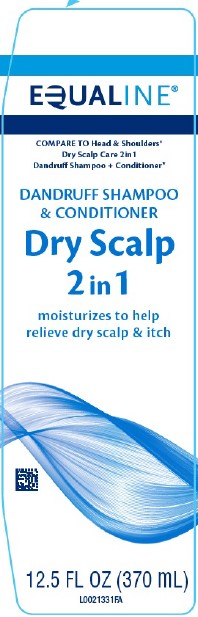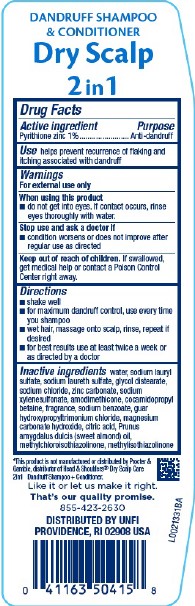 DRUG LABEL: Dry Scalp Care
NDC: 41163-296 | Form: SHAMPOO
Manufacturer: United Natural Foods, Inc. dba UNFI
Category: otc | Type: HUMAN OTC DRUG LABEL
Date: 20260217

ACTIVE INGREDIENTS: PYRITHIONE ZINC 10 mg/1 mL
INACTIVE INGREDIENTS: GUAR HYDROXYPROPYLTRIMONIUM CHLORIDE (1.7 SUBSTITUENTS PER SACCHARIDE); MAGNESIUM CARBONATE HYDROXIDE; CITRIC ACID MONOHYDRATE; ALMOND OIL; METHYLCHLOROISOTHIAZOLINONE; METHYLISOTHIAZOLINONE; WATER; SODIUM LAURYL SULFATE; SODIUM LAURETH SULFATE; GLYCOL DISTEARATE; SODIUM CHLORIDE; ZINC CARBONATE; SODIUM XYLENESULFONATE; AMODIMETHICONE (800 CST); COCAMIDOPROPYL BETAINE; SODIUM BENZOATE

Equaline 296.007/296AV
Dry Scalp 2 In 1 Dandruff Shampoo

Claims

Dandruff Shampoo & Conditioner

Dry Scalp 2 In 1

Active ingredient

Pyrithione zinc 1%

Purpose

Anti-dandruff

Use

helps prevent recurrence of flaking and itching associated with dandruff

Warnings

For external use only

When using this product

- do not get into eyes. If contact occurs, rinse eyes thoroughly with water.

Stop use and ask a doctor if

- condition worsens or does not improve after regular use as directed

Keep out of reach of children.

If swallowed, get medical help or contact a Poison Control Center right away.

Directions

- shake well
- for maximum dandruff control, use every time you shampoo
- wet hair, massage onto scalp, rinse, repeat if desired
- for best results use at least twice a week or as directed by a doctor

Inactive ingredients

water, sodium lauryl sulfate, sodium laureth sulfate, glycol distearate, sodium chloride, zinc carbonate, sodium xylenesulfonate, amodimethicone, cocamidopropyl betaine, fragrance, sodium benzoate, guar hydroxypropyltrimonium chloride, magnesium carbonate hydroxide, citric acid, Prunus amygdalus dulcis (sweet almond) oil, methylchloroisothiazolinone, methylisothiazolinone

Disclaimer

*This product is not manufactured or distributed by Procter & Gamble, distributor of Head & Shoulders® Dry Scalp Care 2in1 Dandruff Shampoo + Conditioner.

Adverse reactions

Like it or let us make it right.

That's our quality promise.

855-423-2630

DISTRIBUTED BY UNFI

PROVIDENCE, RI 02908 USA

Principal display panel

EQUALINE®

Compare to Head & Shoulders® Dry Scalp Care 2in1 Dandruff Shampoo + Conditioner*

Dandruff Shampoo & Conditioner

Dry Scalp

2 in 1

moisturizes to help relieve dry scalp & itch

12.5 FL OZ (370 mL)